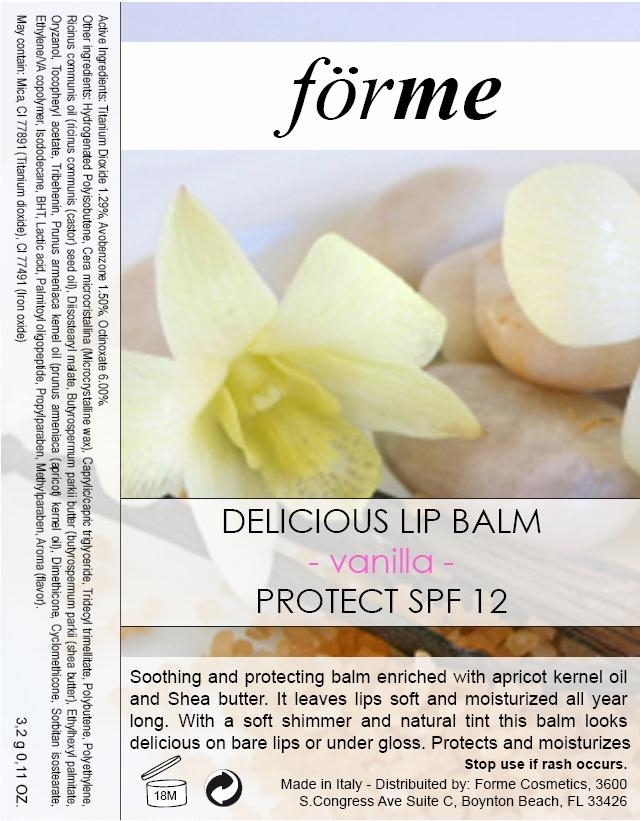 DRUG LABEL: FORME COSMETICS DELICIOUS LIP BALM SPF 12
NDC: 49825-070 | Form: LIPSTICK
Manufacturer: CHROMAVIS SPA
Category: otc | Type: HUMAN OTC DRUG LABEL
Date: 20091013

ACTIVE INGREDIENTS: TITANIUM DIOXIDE 0.04128 g/3.2 g; AVOBENZONE 0.048 g/3.2 g; OCTINOXATE 0.192 g/3.2 g
INACTIVE INGREDIENTS: Lactic Acid

Active Ingredients

Titanium Dioxide 1.29%, Avobenzone 1.50%, Octinoxate 6.00%

PURPOSE

Protect and SPF12

Stop use if rash occurs. As described in the Package Label-principal display area

Other Ingredients

Hydrogenated polyisobutene, Cera microcristallina (Microcrystalline wax), Caprylic/Capric Triglyceride, Tridecyl Trimellitate, Polybutene, Polyethylene, Ricinus Communis oil (ricinus communis (castor) seed oil), Diisostearyl Malate, Butyrospermum Parkii butter (Butyrospermum parkii (shea Butter), Ethylhexyl palmitate, Oryzanol, Tocopheryl acetate, Tribehenin, Prunus armeniaca kernel oil (prunus armeniaca (apricot) kernel oil), Dimethicone, Cyclomethicone, Sorbitan isostearate, Ethylene/VA Copolymer, Isododecane, BHT, Lactic acid, Palmitoyl Oligopeptide, Propylparaben, Methylparaben, Aroma (Flavor)

May Contain: Mica, CI 77891 (Titanium Dioxide), CI 77491 (Iron Oxide)

Refer to the Package Label

PACKAGE LABEL

Forme

Delicious Lip Balm

Vanilla

Protect SPF 12

Stop Use if rash occurs.
Made In Italy- Distributed by Forme Cosmetics, 3600
S. Congress Ave Suite C, Boynton Beach, FL 33426